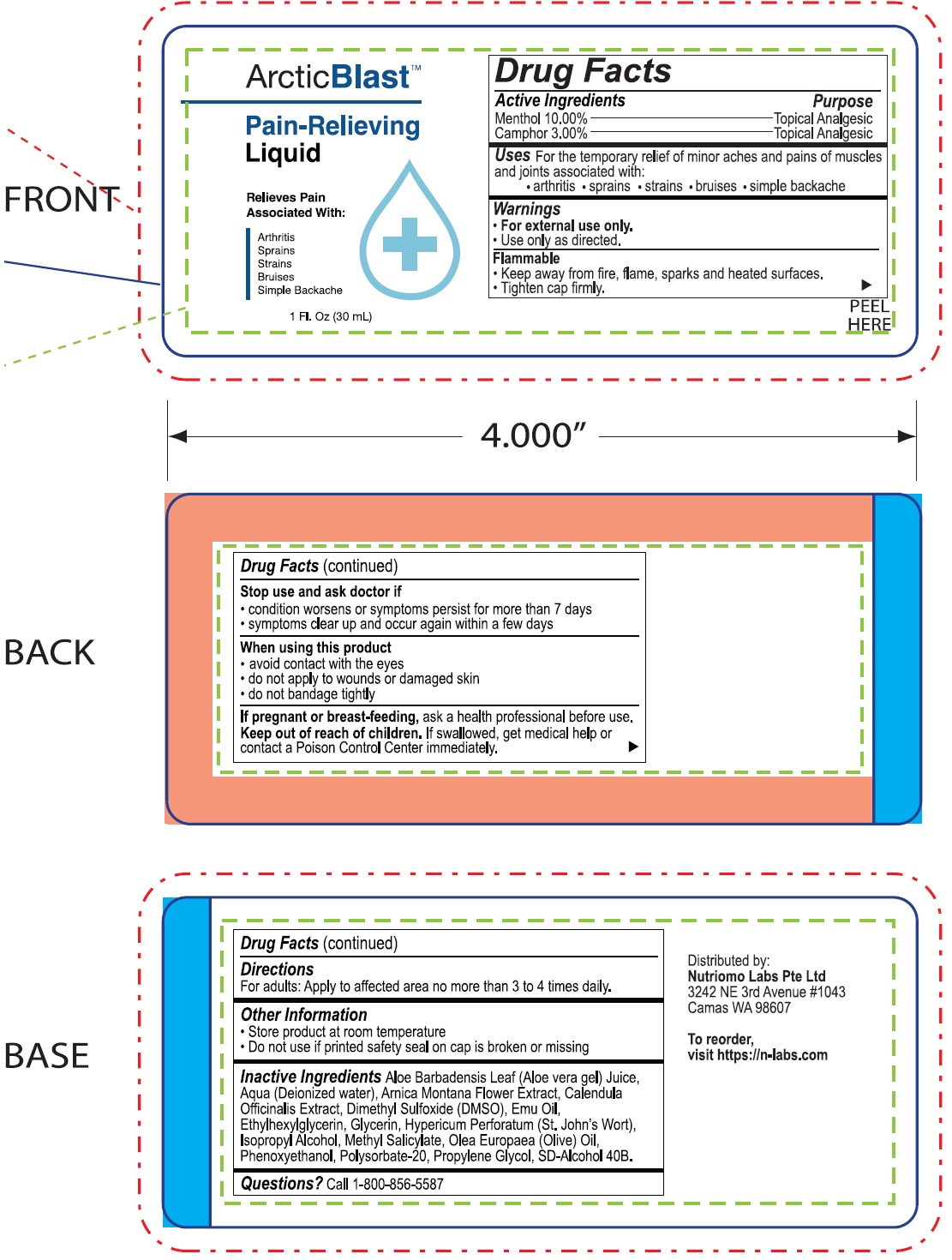 DRUG LABEL: Arctic Blast Pain Releiving
NDC: 71856-176 | Form: LIQUID
Manufacturer: Nutriomo Labs Pte, Ltd
Category: otc | Type: HUMAN OTC DRUG LABEL
Date: 20250310

ACTIVE INGREDIENTS: MENTHOL 100 mg/1 mL; CAMPHOR (SYNTHETIC) 30 mg/1 mL
INACTIVE INGREDIENTS: ALOE VERA LEAF; WATER; ARNICA MONTANA FLOWER; CALENDULA OFFICINALIS FLOWER; DIMETHYL SULFOXIDE; EMU OIL; ETHYLHEXYLGLYCERIN; GLYCERIN; HYPERICUM PERFORATUM WHOLE; ISOPROPYL ALCOHOL; METHYL SALICYLATE; OLEA EUROPAEA (OLIVE) OIL UNSAPONIFIABLES; PHENOXYETHANOL; POLYSORBATE 20; PROPYLENE GLYCOL

Arctic Blast Pain Releiving Drops

Active ingredients

Menthol 10.00%

Camphor 3.00%

Purpose

Topical Analgesic

Indications:

For the temporary relief of minor aches and pains of the muscles and joints associated with: • arthritis • sprains • strains • bruises • simple backache

Warnings

- For external use only.
- Use only as directed.

Flammable

- Keep away from fire, flame, sparks and heated surfaces.
- Tighten cap firmly.

Stop use and ask doctor if

- condition worsens or symptoms persist for more than 7 days
- symptoms clear up and occur again within a few days

When using this product

- avoid contact with the eyes
- do not apply to wounds or damaged skin
- do not bandage tightly

If pregnant or breat-feeding,

ask a health professional before use.

Keep out of reach of children.

If swallowed, get medical help or contact a Poison Control Center immediately.

Directions

For adults: Apply to affected area no more than 3 to 4 times daily.

Other Information

- Store product at room temperature
- Do not use if printed safety seal on cap is broken or missing

Inactive Ingredients

Aloe Barbadensis Leaf (Aloe Vera Gel) Juice, Aqua (Deionized Water), Arnica Montana Flower Extract, Calendula Officinalis Extract, Dimethyl Sulfoxide (DMSO), Emu Oil, Ethylhexylglycerin, Glycerin, Hypericum Perforatum (St. John's Wort), Isopropyl Alcohol, Methyl Salicylate, Olea Europaea (Olive) Oil, Phenoxyethanol, Polysorbate-20, Propylene Glycol, SD-Alcohol 40B.

Questions?

Call 1-800-856-5587